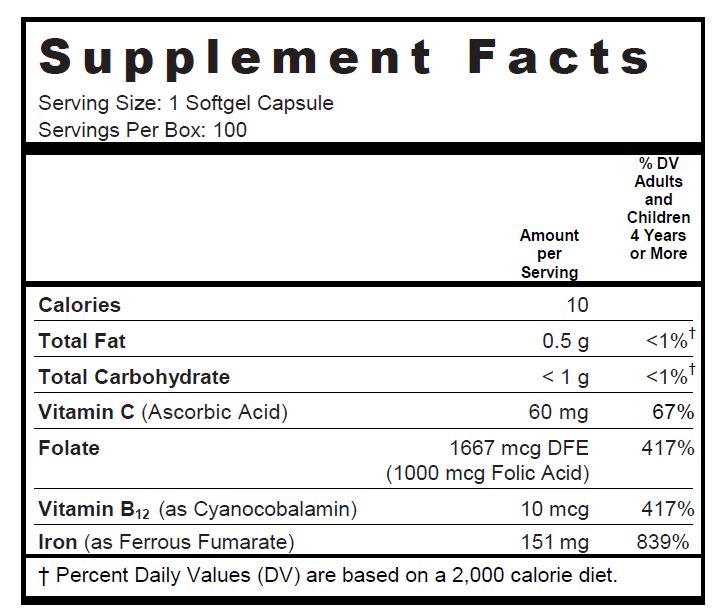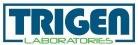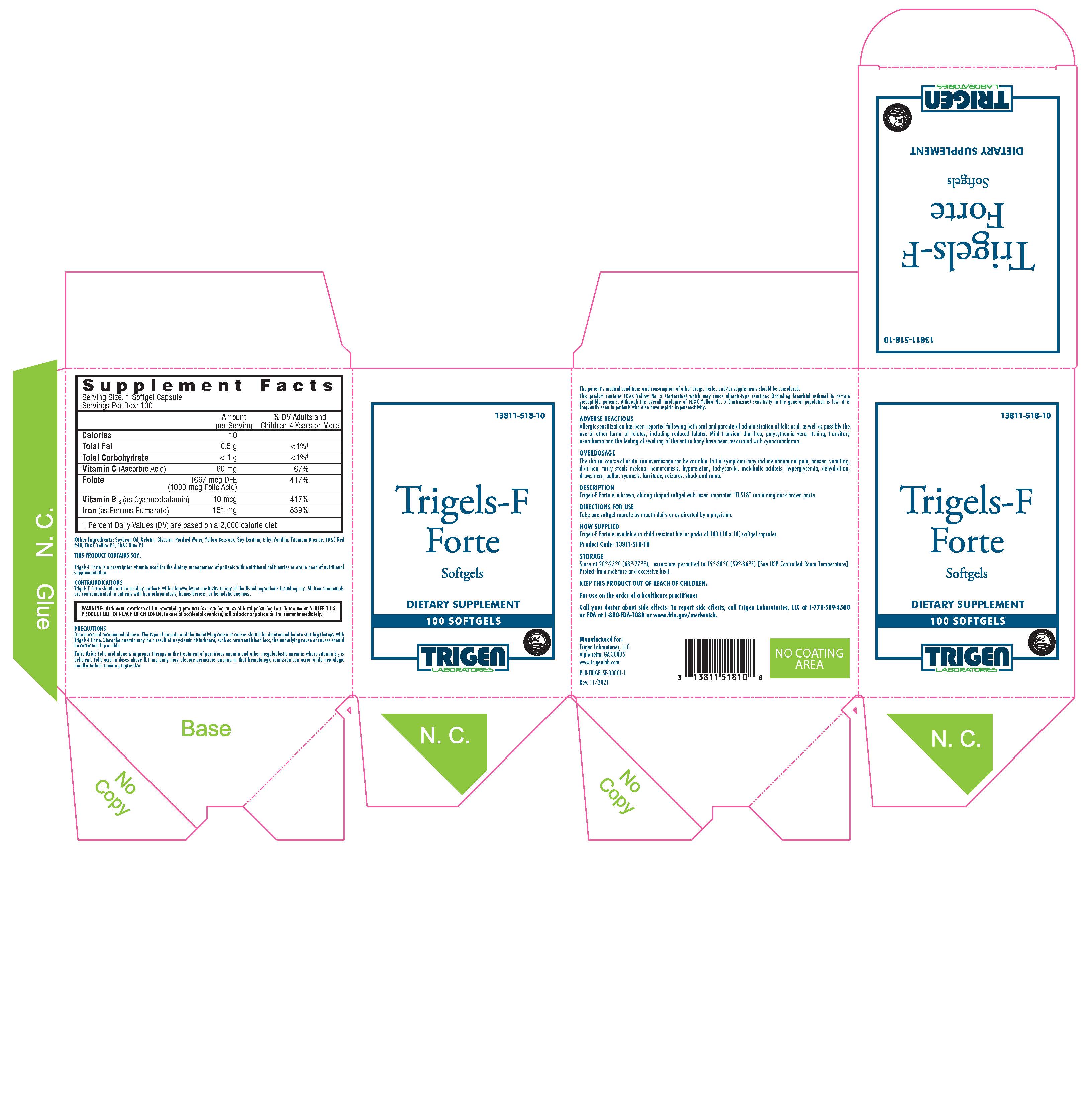 DRUG LABEL: Trigels-F Forte
NDC: 13811-518 | Form: CAPSULE
Manufacturer: Trigen Laboratories, LLC
Category: other | Type: DIETARY SUPPLEMENT
Date: 20211124

ACTIVE INGREDIENTS: Folic Acid 1 mg/1 1; Ascorbic Acid 60 mg/1 1; Cyanocobalamin 10 ug/1 1; Ferrous Fumarate 151 mg/1 1
INACTIVE INGREDIENTS: soybean oil; gelatin; glycerin; water; yellow wax; lecithin, soybean; ethyl vanillin; titanium dioxide; FD&C Red No. 40; FD&C Yellow No. 5; FD&C Blue No. 1

Trigels-F
Forte

DESCRIPTION

Other Ingredients: Soybean Oil, Gelatin, Glycerin, Purified Water, Yellow Beeswax, Soy Lecithin, Ethyl Vanillin, Titanium Dioxide, FD&C Red #40, FD&C Yellow #5, FD&C Blue #1

THIS PRODUCT CONTAINS SOY.

Trigels-F Forte is a prescription vitamin used for the dietary management of patients with nutritional deficiencies or are in need of nutritional supplementation.

Inactive Ingredients

Soybean Oil, Gelatin, Glycerin, Purified Water, Yellow Beeswax, Lecithin, Ethyl Vanillin, Titanium Dioxide, FD&C Red #40, FD&C Yellow #5, FD&C Blue #1.

CONTRAINDICATIONS

Trigels-F Forte should not be used by patients with a known hypersensitivity to any of the listed ingredients including soy. All iron compounds are contraindicated in patients with hemochromatosis, hemosiderosis, or hemolytic anemias.

WARNINGS

WARNING: Accidental overdose of iron-containing products is a leading cause of fatal poisoning in children under 6. KEEP THIS PRODUCT OUT OF REACH OF CHILDREN. In case of accidental overdose, call a doctor or poison control center immediately.

PRECAUTIONS

Do not exceed recommended dose. The type of anemia and the underlying cause or causes should be determined before starting therapy with Trigels-F Forte. Since the anemia may be a result of a systemic disturbance, such as recurrent blood loss, the underlying cause or causes should be corrected, if possible.

Folic Acid: Folic acid alone is improper therapy in the treatment of pernicious anemia and other megaloblastic anemias where vitamin B12 is deficient. Folic acid in doses above 0.1 mg daily may obscure pernicious anemia in that hematologic remission can occur while neurologic manifestations remain progressive.

The patient’s medical conditions and consumption of other drugs, herbs, and/or supplements should be considered.

This product contains FD&C Yellow No. 5 (tartrazine) which may cause allergic-type reactions (including bronchial asthma) in certain susceptible patients. Although the overall incidence of FD&C Yellow No. 5 (tartrazine) sensitivity in the general population is low, it is frequently seen in patients who also have aspirin hypersensitivity.

ADVERSE REACTIONS

Allergic sensitization has been reported following both oral and parenteral administration of folic acid, as well as possibly the use of other forms of folates, including reduced folates. Mild transient diarrhea, polycythemia vera, itching, transitory exanthema and the feeling of swelling of the entire body have been associated with cyanocobalamin.

OVERDOSAGE

The clinical course of acute iron overdosage can be variable. Initial symptoms may include abdominal pain, nausea, vomiting, diarrhea, tarry stools melena, hematemesis, hypotension, tachycardia, metabolic acidosis, hyperglycemia, dehydration, drowsiness, pallor, cyanosis, lassitude, seizures, shock and coma.

DESCRIPTION

Trigels-F Forte is a brown, oblong shaped softgel with laser imprinted “TL518” containing dark brown paste.

DIRECTIONS FOR USE

Take one softgel capsule by mouth daily or as directed by a physician.

HOW SUPPLIED

Trigels-F Forte is available in child resistant blister packs of 100 (10 x 10) softgel capsules.

Product Code: 13811-518-10

STORAGE

Store at 20°-25°C (68°-77°F), excursions permitted to 15°-30°C (59°-86°F) [See USP Controlled Room Temperature]. Protect from moisture and excessive heat.

HEALTH CLAIM

KEEP THIS PRODUCT OUT OF REACH OF CHILDREN.

For use on the order of a healthcare practitioner

Call your doctor about side effects. To report side effects, call Trigen Laboratories, LLC at 1-770-509-4500 or FDA at
1-800-FDA-1088 or www.fda.gov/medwatch.

PLR-TRIGELSF-00001-1 Rev. 11/2021

Manufactured for:
Trigen Laboratories, LLC
Alpharetta, GA 30005
www.trigenlab.com

PRINCIPAL DISPLAY PANEL - 100 Softgel Blister Pack Carton

13811-518-10

Trigels-F
Forte

Softgels

100 SOFTGELS

TRIGEN
LABORATORIES